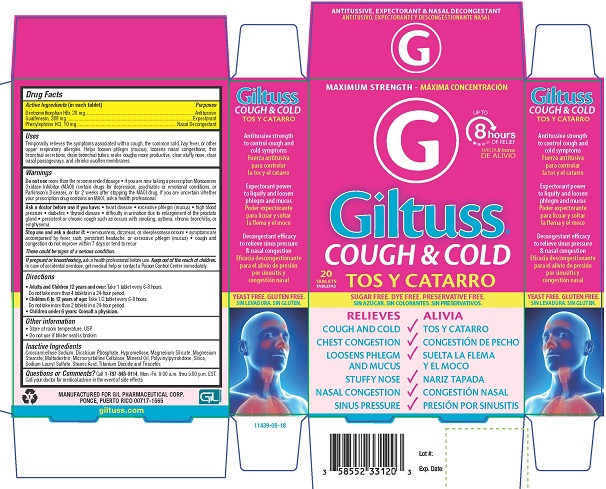 DRUG LABEL: Giltuss Cough and Cold
NDC: 58552-331 | Form: TABLET
Manufacturer: Gil Pharmaceutical Corp
Category: otc | Type: HUMAN OTC DRUG LABEL
Date: 20251009

ACTIVE INGREDIENTS: GUAIFENESIN 388 mg/1 1; DEXTROMETHORPHAN HYDROBROMIDE 28 mg/1 1; PHENYLEPHRINE HYDROCHLORIDE 10 mg/1 1
INACTIVE INGREDIENTS: CALCIUM PHOSPHATE, DIBASIC, DIHYDRATE; HYPROMELLOSE, UNSPECIFIED; MAGNESIUM STEARATE; MALTODEXTRIN; CELLULOSE, MICROCRYSTALLINE; LIGHT MINERAL OIL; POVIDONE K30; SILICON DIOXIDE; SODIUM LAURYL SULFATE; STEARIC ACID; TITANIUM DIOXIDE; TRIACETIN; TALC; CROSCARMELLOSE SODIUM

4060-Giltuss Cough & Cold Tablets

Drug Facts

Active Ingredients (in each tablet)

Dextromethorphan HBr, 28 mg

Guaifenesin, 388 mg

Phenylephrine HCl, 10 mg

Purposes

Antitussive

Expectorant

Nasal Decongestant

Uses

Temporarily relieves the symptoms associated with a cough, the common cold, hay fever, or other upper respiratory allergies. Helps loosen phlegm (mucus), loosens nasal congestion, thin bronchial secretions, drain bronchial tubes, make coughs more productive, clear stuffy nose, clear nasal passageways, and shrinks swollen membranes.

Warnings

Do not usemore than the recommended dosage

- or if you are now taking a prescription Monoamine Oxidase Inhibitor (MAOI) (certain drugs for depression, psychiatric or emotional conditions, or Parkinson’s Disease), or for 2 weeks after stopping the MAOI drug. If you are uncertain whether your prescription drug contains an MAOI, ask a health professional.

Ask a doctor before use if you have:

- heart disease
- excessive phlegm (mucus)
- high blood pressure
- diabetes
- thyroid disease
- difficulty in urination due to enlargement of the prostate gland
- persistent or chronic cough such as occurs with smoking, asthma, chronic bronchitis, or emphysema

Stop use and ask a doctor if:

- nervousness, dizziness, or sleeplessness occurs
- symptoms are accompanied by fever, rash, persistent headache, or excessive phlegm (mucus)
- cough and congestion do not improve within 7 days or tend to recur

These could be signs of a serious condition.

PREGNANCY OR BREAST FEEDING

If pregnant or breast-feeding,ask a health professional before use.

KEEP OUT OF REACH OF CHILDREN

Keep out of the reach of children.In case of accidental overdose, get medical help or contact a Poison Control Center immediately.

Directions

• Adults and Children 12 years and over:Take 1 tablet every 6 to 8 hours. Do not take more than 4 tablets in a 24 hour period.

• Children 6 to 12 years of age:Take 1/2 tablet every 6 to 8 hours. Do not take more than 2 tablets in a 24-hour period.

• Children under 6 years of age: Consult a physician.

Other information

- Store at room temperature, USP
- Do not use if blister seal is broken

INACTIVE INGREDIENT

Inactive ingredientsCroscarmellose Sodium, Dicalcium Phosphate, Hypromellose, Magnesium Silicate, Magnesium Stearate, Maltodextrin, Microcrystalline Cellulose, Mineral Oil, Polyvinylpyrrolidone, Silica, Sodium Lauryl Sulfate, Stearic Acid, Titanium Dioxide and Triacetin.

Questions or Comments?Call 787-848-9114, Mon.-Fri. 9:00 a.m. thru 5:00 p.m. EST. Call your doctor for medical advice in the event of side effects.

MANUFACTURED FOR GIL PHARMACEUTICAL CORP.

PONCE, PUERTO RICO 00717-1565

giltuss.com

PACKAGE LABEL

MAXIMUM STRENGTH

Giltuss ®

COUGH & COLD

20 TABLETS
SUGAR FREE. DYE FREE. PRESERVATIVE FREE.

RELIEVES

- COUGH AND COLD
- CHEST CONGESTION
- LOOSENS PHLEGM AND MUCUS
- STUFFY NOSE
- NASAL CONGESTION
- SINUS PRESSURE